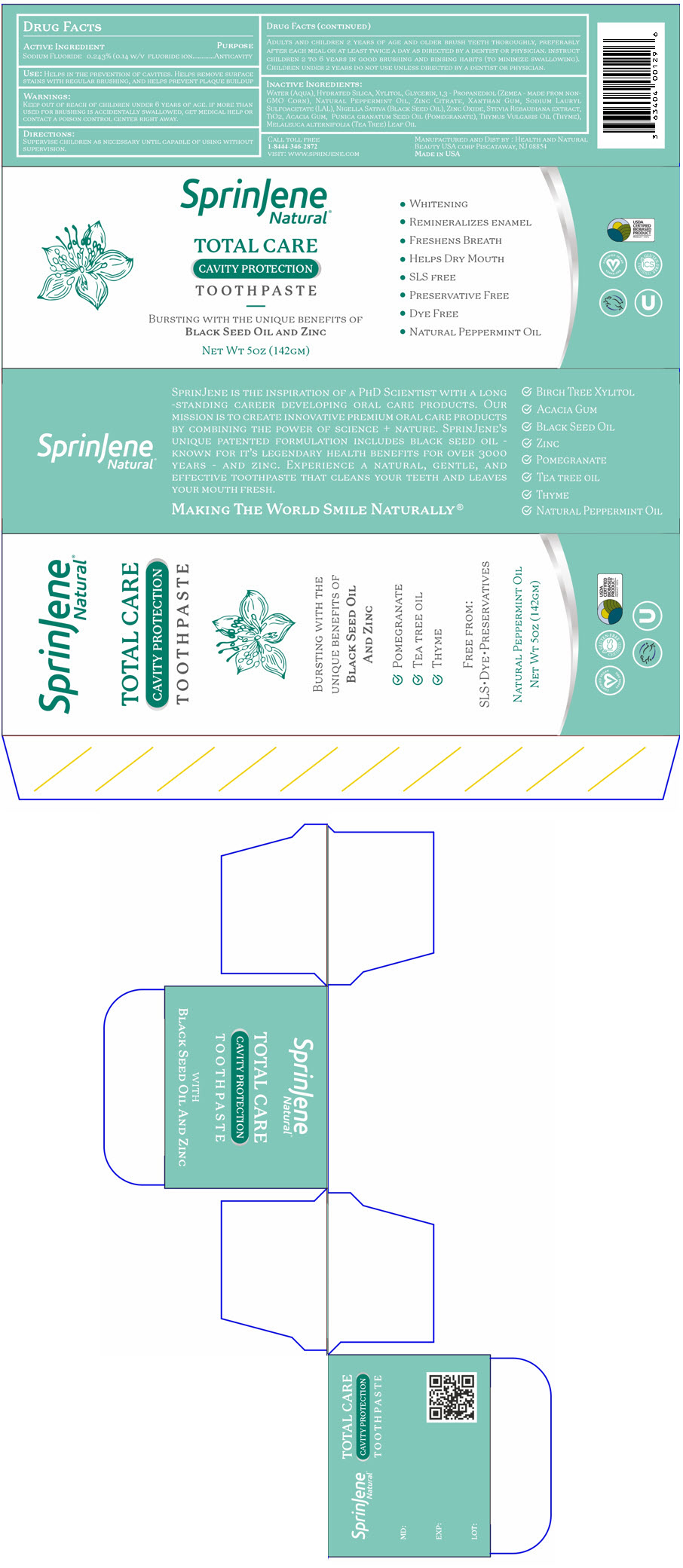 DRUG LABEL: SprinJene 
NDC: 63404-6319 | Form: PASTE, DENTIFRICE
Manufacturer: Health and Natural Beauty USA Corp
Category: otc | Type: HUMAN OTC DRUG LABEL
Date: 20240507

ACTIVE INGREDIENTS: SODIUM FLUORIDE 1.5 mg/1 g
INACTIVE INGREDIENTS: WATER; Hydrated Silica; Glycerin; Xylitol; PROPANEDIOL; Xanthan Gum; Zinc Citrate; Cocamidopropyl Hydroxysultaine; Sodium Hydroxide; Titanium Dioxide; ACACIA; ECHINACEA PURPUREA WHOLE; SALVIA ROSMARINUS FLOWERING TOP; THYME OIL; GOLDENSEAL

SprinJene
Natural® Total Care Cavity Protection

DRUG FACTS

ACTIVE INGREDIENT

SODIUM FLUORIDE 0.243% (0.14 W/V FLUORIDE ION

PURPOSE

ANTICAVITY

USE

HELPS IN THE PREVENTION OF CAVITIES. HELPS REMOVE SURFACE STAINS WITH REGULAR BRUSHING, AND HELPS PREVENT PLAQUE BUILDUP

WARNINGS

KEEP OUT OF REACH OF CHILDREN UNDER 6 YEARS OF AGE. IF MORE THAN USED FOR BRUSHING IS ACCIDENTALLY SWALLOWED, GET MEDICAL HELP OR CONTACT A POISON CONTROL CENTER RIGHT AWAY.

DIRECTIONS

SUPERVISE CHILDREN AS NECESSARY UNTIL CAPABLE OF USING WITHOUT SUPERVISION.

ADULTS AND CHILDREN 2 YEARS OF AGE AND OLDER BRUSH TEETH THOROUGHLY, PREFERABLY AFTER EACH MEAL OR AT LEAST TWICE A DAY AS DIRECTED BY A DENTIST OR PHYSICIAN. INSTRUCT CHILDREN 2 TO 6 YEARS IN GOOD BRUSHING AND RINSING HABITS (TO MINIMIZE SWALLOWING). CHILDREN UNDER 2 YEARS DO NOT USE UNLESS DIRECTED BY A DENTIST OR PHYSICIAN.

INACTIVE INGREDIENTS

WATER (AQUA), HYDRATED SILICA, XYLITOL, GLYCERIN, 1,3 - PROPANEDIOL (ZEMEA - MADE FROM NON-GMO CORN), NATURAL PEPPERMINT OIL, ZINC CITRATE, XANTHAN GUM, SODIUM LAURYL SULFOACETATE (LAL), NIGELLA SATIVA (BLACK SEED OIL), ZINC OXIDE, STEVIA REBAUDIANA EXTRACT, TIO2, ACACIA GUM, PUNICA GRANATUM SEED OIL (POMEGRANATE), THYMUS VULGARIS OIL (THYME), MELALEUCA ALTERNIFOLIA (TEA TREE) LEAF OIL

MANUFACTURED AND DIST BY : HEALTH AND NATURAL
BEAUTY USA CORP PISCATAWAY, NJ 08854

PRINCIPAL DISPLAY PANEL - 142 GM Tube Carton

SprinJene
Natural®

TOTAL CARE
CAVITY PROTECTION
TOOTHPASTE

BURSTING WITH THE UNIQUE BENEFITS OF
BLACK SEED OIL AND ZINC

NET WT 5OZ (142GM)

- WHITENING
- REMINERALIZES ENAMEL
- FRESHENS BREATH
- HELPS DRY MOUTH
- SLS FREE
- PRESERVATIVE FREE
- DYE FREE
- NATURAL PEPPERMINT OIL

USDA
CERTIFIED
BIOBASED
PRODUCT
PRODUCT 100%

CERTIFIED VEGAN
VEGAN.ORG

GLUTEN-FREE
CERTIFIED